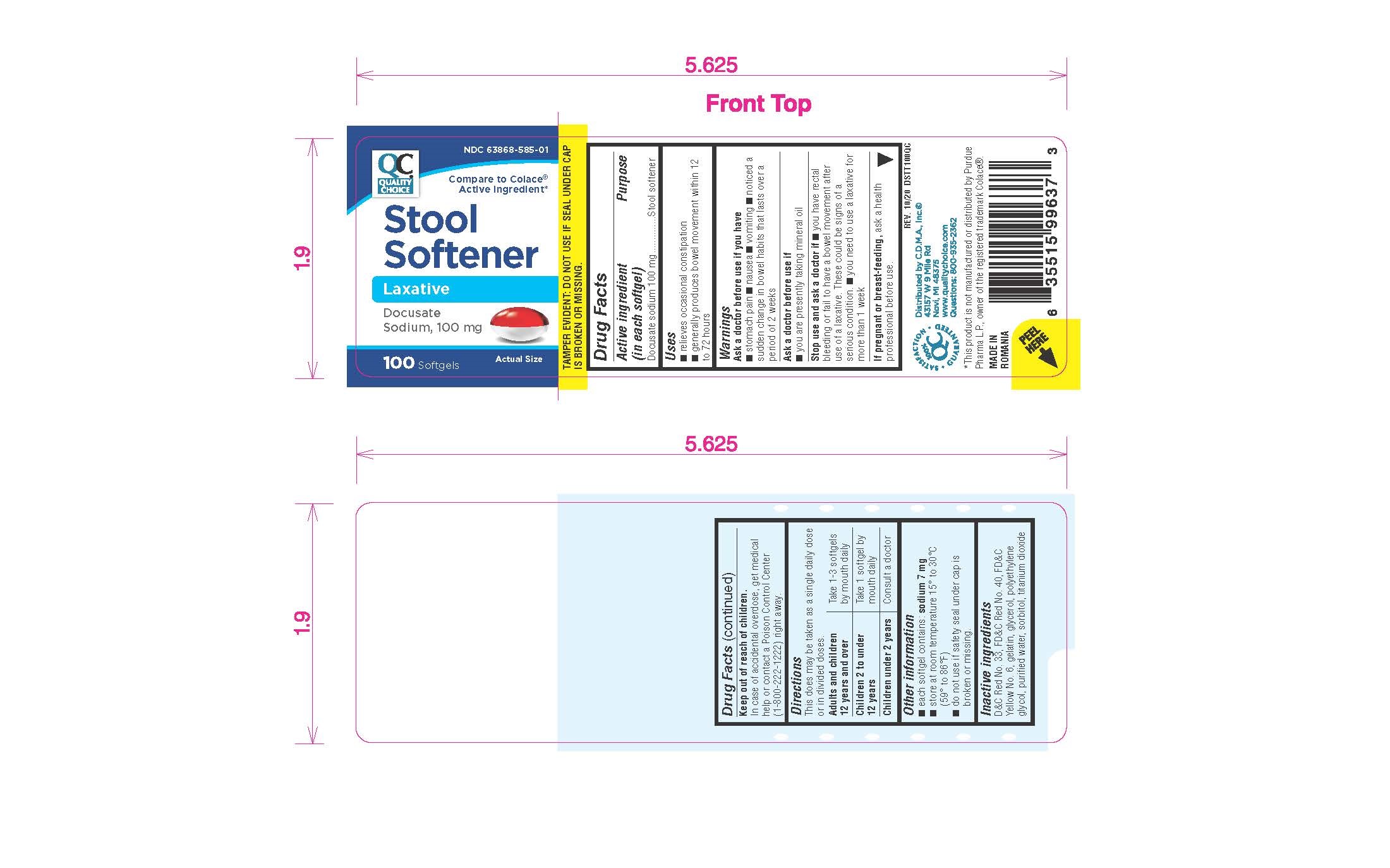 DRUG LABEL: Quality Choice Stool Softener
NDC: 83324-197 | Form: CAPSULE, LIQUID FILLED
Manufacturer: Chain Drug Marketing Association
Category: otc | Type: HUMAN OTC DRUG LABEL
Date: 20251202

ACTIVE INGREDIENTS: DOCUSATE SODIUM 100 mg/1 1
INACTIVE INGREDIENTS: ANHYDROUS CITRIC ACID; D&C RED NO. 33; FD&C BLUE NO. 1; FD&C RED NO. 40; FD&C YELLOW NO. 6; GELATIN; GLYCERIN; POLYETHYLENE GLYCOL, UNSPECIFIED; PROPYLENE GLYCOL; SORBITOL; WATER

DOCUSATE SODIUM 100mg Two-Tone, Capsule, liquid filled

Drug Facts

Active ingredient (in each softgel)

Docusate Sodium 100 mg

Purpose

Stool softener

Uses

- relieves occasional constipation (irregularity)
- generally produces a bowel movement in 12 to 72 hours

Warnings

Do not use

- if you are presently taking mineral oil, unless told to do so by a doctor

Ask a doctor before use if you have

- stomach pain
- nausea
- vomiting
- noticed a sudden change in bowel movements that lasts over 2 weeks

Stop use and ask a doctor if

- you have rectal bleeding or fail to have a bowel movement after use of a laxative. These could be signs of a serious condition.
- you need to use a stool softener laxative for more than 1 week

PREGNANCY OR BREAST FEEDING

If pregnant or breast-feeding, ask a health professional before use.

Keep out of reach of children. In case of overdose, get medical help or contact a Poison Control Center right away.

Directions

Take only by mouth. Doses may be taken as a single daily dose or in divided doses.

adults and children 12 years and over | take 1 to 3 softgels daily
children 2 to under 12 years of age | take 1 softgel daily
children under 2 years | ask a doctor

Other information

- each softgel contains: sodium 5 mg
- VERY LOW SODIUM
- store at room temperature 15°-30°C (59°-86°F) and avoid excessive heat

Inactive Ingredients

D&C Red No. 33, FD&C Red No. 40, FD&C Yellow No. 6, gelatin, glycerol, Polyethylene glycol, purified water, sorbitol, titanium dioxide